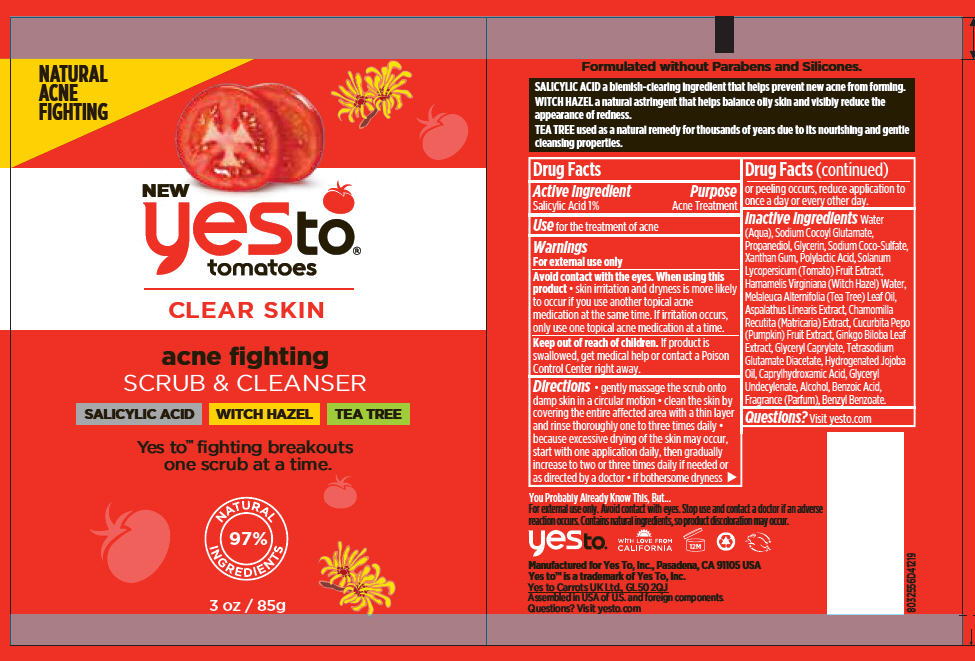 DRUG LABEL: Yes To Tomatoes Acne Fighting Scrub and Cleanser
NDC: 69840-015 | Form: SUSPENSION
Manufacturer: Yes To, Inc.
Category: otc | Type: HUMAN OTC DRUG LABEL
Date: 20190429

ACTIVE INGREDIENTS: SALICYLIC ACID 10 mg/1 g
INACTIVE INGREDIENTS: WATER; SODIUM COCOYL GLUTAMATE; PROPANEDIOL; GLYCERIN; SODIUM COCO-SULFATE; XANTHAN GUM; POLYLACTIDE; HAMAMELIS VIRGINIANA TOP WATER; GLYCERYL MONOCAPRYLATE; HYDROGENATED JOJOBA OIL; TETRASODIUM GLUTAMATE DIACETATE; SOLANUM LYCOPERSICUM; TEA TREE OIL; CAPRYLHYDROXAMIC ACID; GLYCERYL 1-UNDECYLENATE; ALCOHOL; ASPALATHUS LINEARIS LEAF; MATRICARIA CHAMOMILLA; PUMPKIN; GINKGO; BENZOIC ACID

Yes To® Tomatoes Acne Fighting Scrub & Cleanser

Drug Facts

Active Ingredient

Salicylic Acid 1%

Purpose

Acne Treatment

Use

for the treatment of acne

Warnings

For external use only

WHEN USING

Avoid contact with the eyes. When using this product

- skin irritation and dryness is more likely to occur if you use another topical acne medication at the same time. If irritation occurs, only use one topical acne medication at a time.

Keep out of reach of children. If product is swallowed, get medical help or contact a Poison Control Center right away.

Directions

- gently massage the scrub onto damp skin in a circular motion
- clean the skin by covering the entire affected area with a thin layer and rinse thoroughly one to three times daily
- because excessive drying of the skin may occur, start with one application daily, then gradually increase to two or three times daily if needed or as directed by a doctor
- if bothersome dryness or peeling occurs, reduce application to once a day or every other day.

Inactive Ingredients

(Aqua), Sodium Cocoyl Glutamate, Propanediol, Glycerin, Sodium Coco-Sulfate, Xanthan Gum, Polylactic Acid, Solanum Lycopersicum (Tomato) Fruit Extract, Hamamelis Virginiana (Witch Hazel) Water, Melaleuca Alternifolia (Tea Tree) Leaf Oil, Aspalathus Linearis Extract, Chamomilla Recutita (Matricaria) Extract, Cucurbita Pepo (Pumpkin) Fruit Extract, Ginkgo Biloba Leaf Extract, Glyceryl Caprylate, Tetrasodium Glutamate Diacetate, Hydrogenated Jojoba Oil, Caprylhydroxamic Acid, Glyceryl Undecylenate, Alcohol, Benzoic Acid, Fragrance (Parfum), Benzyl Benzoate.

Questions?

Visit yesto.com

PRINCIPAL DISPLAY PANEL - 85 g Tube Label

NATURAL
ACNE
FIGHTING

NEW
yesto®
tomatoes

CLEAR SKIN

acne fighting
SCRUB & CLEANSER

SALICYLIC ACID
WITCH HAZEL
TEA TREE

Yes to™ fighting breakouts
one scrub at a time.

NATURAL
97%
INGREDIENTS

3 oz / 85g